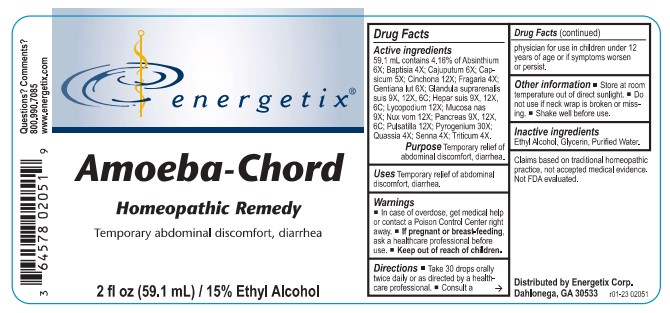 DRUG LABEL: Amoeba-Chord
NDC: 64578-0058 | Form: LIQUID
Manufacturer: Energetix Corporation
Category: homeopathic | Type: HUMAN OTC DRUG LABEL
Date: 20241120

ACTIVE INGREDIENTS: WORMWOOD 6 [hp_X]/1 mL; BAPTISIA TINCTORIA ROOT 4 [hp_X]/1 mL; CAJUPUT OIL 6 [hp_X]/1 mL; CAPSICUM 5 [hp_X]/1 mL; CINCHONA OFFICINALIS BARK 12 [hp_X]/1 mL; ALPINE STRAWBERRY 4 [hp_X]/1 mL; GENTIANA LUTEA ROOT 6 [hp_X]/1 mL; SUS SCROFA ADRENAL GLAND 9 [hp_X]/1 mL; PORK LIVER 9 [hp_X]/1 mL; LYCOPODIUM CLAVATUM SPORE 12 [hp_X]/1 mL; SUS SCROFA NASAL MUCOSA 9 [hp_X]/1 mL; STRYCHNOS NUX-VOMICA SEED 12 [hp_X]/1 mL; SUS SCROFA PANCREAS 9 [hp_X]/1 mL; PULSATILLA VULGARIS 12 [hp_X]/1 mL; RANCID BEEF 30 [hp_X]/1 mL; QUASSIA AMARA WOOD 4 [hp_X]/1 mL; SENNA LEAF 4 [hp_X]/1 mL; ELYMUS REPENS ROOT 4 [hp_X]/1 mL
INACTIVE INGREDIENTS: WATER; GLYCERIN; ALCOHOL

Amoeba-Chord

Active ingredients

59.1 mL contains 4.16% of Absinthium 6X; Baptisia 4X; Cajuputum 6X; Capsicum 5X; Cinchona 12X; Fragaria 4X; Gentiana lut 6X; Glandula suprarenalis suis 9X, 12X, 6C; Hepar suis 9X, 12X, 6C; Lycopodium 12X; Mucosa nas 9X; Nux vom 12X; Pancreas 9X, 12X, 6C; Pulsatilla 12X; Pyrogenium 30X; Quassia 4X; Senna 4X; Triticum 4X.

Claims based on traditional homeopathic practice, not accepted medical evidence. Not FDA evaluated.

Uses

Temporary relief of abdominal discomfort, diarrhea.

Warnings

- In case of overdose, get medical help or contact a Poison Control Center right away.
- If pregnant or breast feeding,ask a health professional before use.

- Keep out of reach of children.

DIRECTIONS:

- Take 30 drops orally twice daily or as directed by a healthcare professional.
- Consult a physician for use in children under 12 years of age or if symptoms worsen or persist.

Other information

- Store at room temperature out of direct sunlight.
- Do not use if neck wrap is broken or missing.
- Shake well before use.

Inactive ingredients

Ethyl Alcohol, Glycerin, Purified Water.

QUESTIONS

Distributed by Energetix Corp.

Dahloneha, GA 30533

Questions? Comments?

800.990.7085

www.energetix.com

PACKAGE LABEL

energetix

Amoeba-Chord

Homeopathic Remedy

Temporary abdominal discomfort, diarrhea

2 fl oz (59.1 mL) / 15% Ethyl Alcohol

Purpose

Temporary relief of abdominal discomfort, diarrhea.